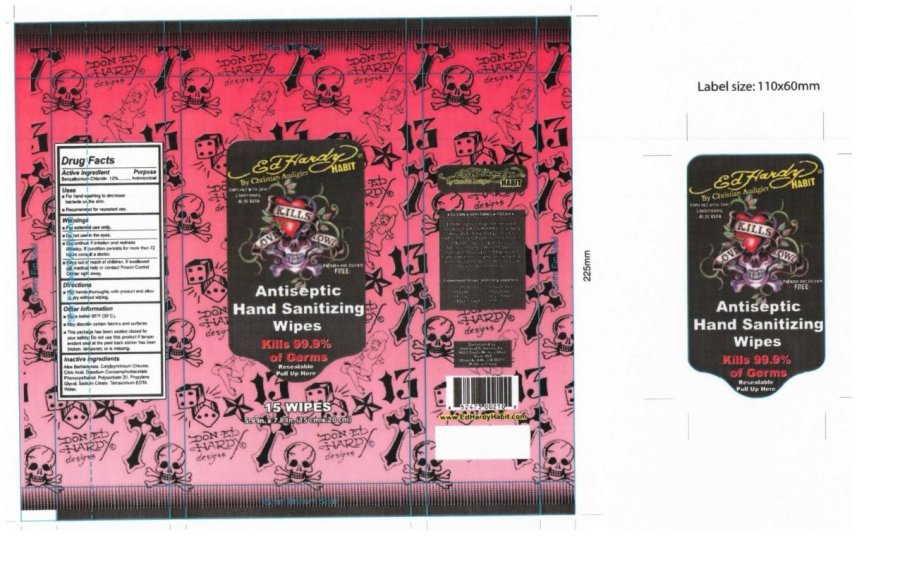 DRUG LABEL: Ed Hardy Habit Antiseptic Hand Sanitizing Wipe
NDC: 50078-201 | Form: SWAB
Manufacturer: Ed Hardy Habit 
Category: otc | Type: HUMAN OTC DRUG LABEL
Date: 20091209

ACTIVE INGREDIENTS: BENZALKONIUM CHLORIDE 0.12 1/1 1
INACTIVE INGREDIENTS: ALOE VERA FLOWER; CETYLPYRIDINIUM CHLORIDE; CITRIC ACID MONOHYDRATE; PHENOXYETHANOL; POLYSORBATE 20; PROPYLENE GLYCOL; SODIUM CITRATE; WATER

Ed Hardy Habit Antiseptic Hand Sanitizing Wipes 15 wipes

Active Ingredient Purpose

Benzalkonium Chloride .12percent Antimicrobial

Uses

For hand washing to decrease bacteria on the skin.

Recommended for repeated use.

Warnings

For external use only.

Do not use in the eyes.

Discontinue if irritation and redness develop.

If condition persists for more than 72 hours consult a doctor.

Keep out of the reach of children .

If swallowed get medical help or contact Poison Control Center right away.

Directions

Wet hands thoroughly with product and allow to dry without wiping.

Other Information

Store below 92 degrees F - 35 degrees C

May discolor certain fabrics and surfaces.

This package has been sealed closed for your safety.

Do not use this product if tamper evident seal at the peel back sticker has been broken, tampered, or is missing.

Inactive Ingredients

Aloe Barbadensis, Cetylpyrdinium Chloride, Citric Acid, Disodium Cocoamphodiacetate,

Phenoxyethanol, Polysorbate 20, Propylene Glycol, Sodium Citrate, Tetrasodium EDTA, Water

PACKAGE LABEL

Ed Hardy Habit
by Christian Audigier
Paraben And Sulfate Free
Enriched With Skin Conditioning Aloe Vera
Antiseptic Hand Sanitizing Wipes
Kills 99.9 percent of Germs
Resealable
Pull Up Here
15 Wipes
5.9 In by 7.8 In (15 cm x 20cm)
Clean Soothing Fresh
Introducing the vintage tattoo-inspired sensation, Ed Hardy Habit Sanitizing Wipes by Christian Audigier
A color explosion of fruity floral essence with a rock' roll sexy edge. Using the wipes is a a delicious
and very addictive fragranced Habit. Use theses wipes to kill germs and bacteria while moisturizing your skin
with an aloe soothing formula. The thick wipes are great for cleansing hands.
Convenient to use and carry anywhere
School desk
Locker
Purse
Back Pocket
Diaper Bag
Backpack
Lunch Box
Office